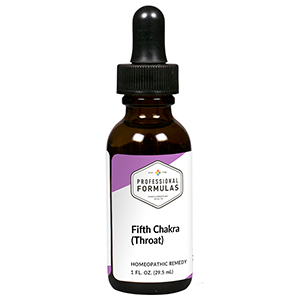 DRUG LABEL: Fifth Chakra (Throat)
NDC: 63083-7305 | Form: LIQUID
Manufacturer: Professional Complementary Health Formulas
Category: homeopathic | Type: HUMAN OTC DRUG LABEL
Date: 20190815

ACTIVE INGREDIENTS: ANHYDROUS DIBASIC CALCIUM PHOSPHATE 8 [hp_X]/29.5 mL; SODIUM SULFATE 8 [hp_X]/29.5 mL; SILICON DIOXIDE 8 [hp_X]/29.5 mL; SPIGELIA ANTHELMIA WHOLE 8 [hp_X]/29.5 mL; COLCHICUM AUTUMNALE BULB 12 [hp_X]/29.5 mL; NAJA NAJA VENOM 12 [hp_X]/29.5 mL; NERIUM OLEANDER WHOLE 12 [hp_X]/29.5 mL; CARBO ANIMALIS 15 [hp_X]/29.5 mL; CORALLIUM RUBRUM EXOSKELETON 15 [hp_X]/29.5 mL; CALCIUM HEXAFLUOROSILICATE 30 [hp_X]/29.5 mL; MALACHITE GREEN 30 [hp_X]/29.5 mL; SODIUM 30 [hp_X]/29.5 mL
INACTIVE INGREDIENTS: ALCOHOL; WATER

RCT5

ACTIVE INGREDIENTS

Calcarea phosphorica 8X
Natrum sulphuricum 8X
Silicea 8X
Spigelia anthelmia 8X
Colchicum autumnale 12X
Naja tripudians 12X
Oleander 12X
Carbo animalis 15X
Corallium rubrum 15X
Lapis lazuli 30X, 60X, 100X
Malachite 30X, 60X, 100X
Rose quartz 30X, 60X, 100X
Sodalite 30X, 60X, 100X
Turquoise 30X, 60X, 100X

QUESTIONS

Professional Formulas

PO Box 2034 Lake Oswego, OR 97035

INDICATIONS

Temporarily relieves arrogance, shyness, fear of speaking, inability to express thoughts or feelings, social anxiousness, stubbornness, or fear of being detached from others.*

PURPOSE

*Claims based on traditional homeopathic practice, not accepted medical evidence. Not FDA evaluated.

WARNINGS

In case of overdose, get medical help or contact a poison control center right away.

Keep out of the reach of children.

PREGNANCY OR BREAST FEEDING

If pregnant or breastfeeding, ask a healthcare professional before use.

DIRECTIONS

Place drops under tongue 30 minutes before/after meals. Adults and children 12 years and over: Take 5 drops up to 4 times per day for up to one month. Consult a physician for use in children under 12 years of age.

OTHER INFORMATION

Tamper resistant. If seal is broken, do not use. After opening, close container tightly and store at room temperature away from heat.

INACTIVE INGREDIENTS

20% ethanol, purified water.

LABEL

Est 1985

Professional Formulas

Complementary Health

Fifth Chakra (Throat)

Homeopathic Remedy

1 FL. OZ. (29.5 mL)